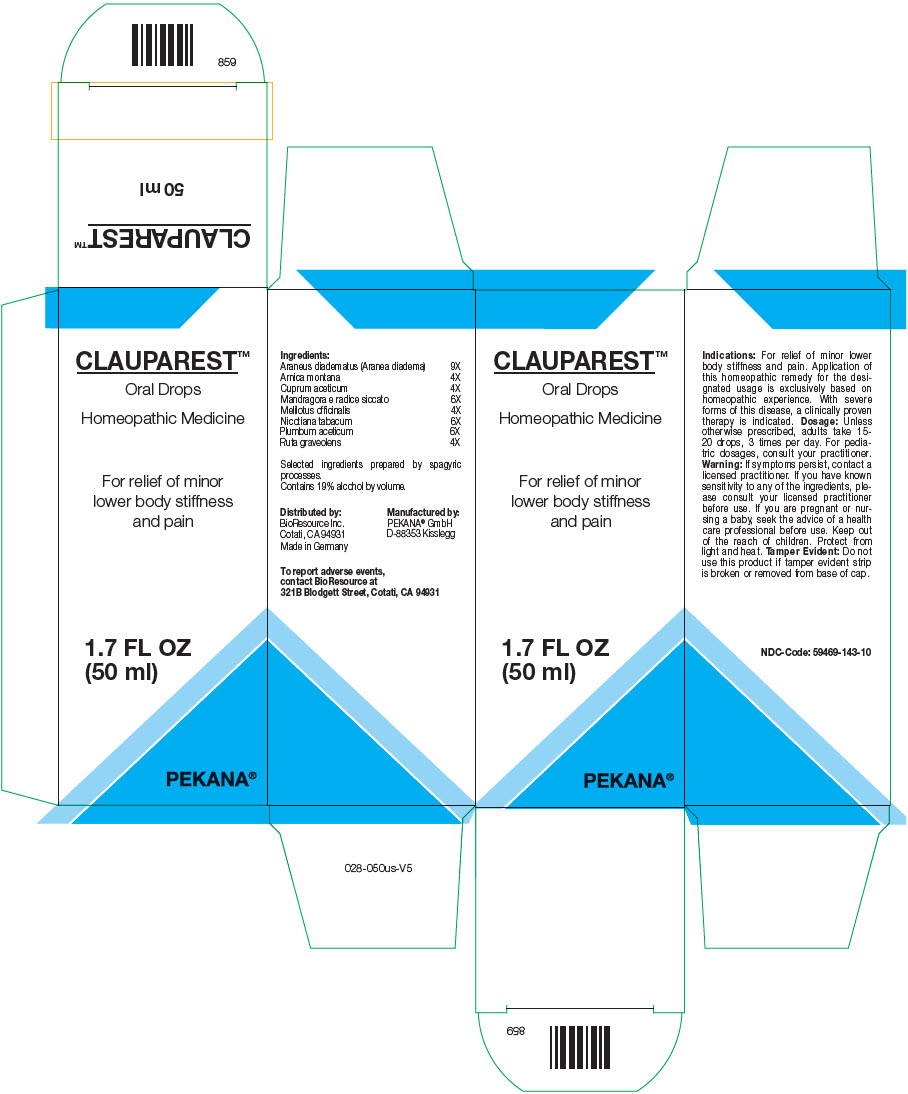 DRUG LABEL: CLAUPAREST
NDC: 59469-143 | Form: SOLUTION/ DROPS
Manufacturer: PEKANA Naturheilmittel GmbH
Category: homeopathic | Type: HUMAN OTC DRUG LABEL
Date: 20221206

ACTIVE INGREDIENTS: Araneus diadematus 9 [hp_X]/50 mL; Arnica montana Root 4 [hp_X]/50 mL; Cupric Acetate 4 [hp_X]/50 mL; Mandragora officinarum Root 6 [hp_X]/50 mL; Lead Acetate Anhydrous 6 [hp_X]/50 mL; Tobacco Leaf 6 [hp_X]/50 mL; Melilotus officinalis Top 4 [hp_X]/50 mL; Ruta graveolens Flowering Top 4 [hp_X]/50 mL
INACTIVE INGREDIENTS: Water; Alcohol

CLAUPAREST™

ACTIVE INGREDIENT

Ingredients:
Araneus diadematus (Aranea diadema) | 9X
Arnica montana | 4X
Cuprum aceticum | 4X
Mandragora e radice siccato | 6X
Melilotus officinalis | 4X
Nicotiana tabacum | 6X
Plumbum aceticum | 6X
Ruta graveolens | 4X

Selected ingredients prepared by spagyric processes.

INACTIVE INGREDIENT

Contains 19% alcohol by volume.

Indications

PURPOSE

For relief of minor lower body stiffness and pain. Application of this homeopathic remedy for the designated usage is exclusively based on homeopathic experience. With severe forms of this disease, a clinically proven therapy is indicated.

Dosage

Unless otherwise prescribed, adults take 15-20 drops, 3 times per day. For pediatric dosages, consult your practitioner.

Warning

If symptoms persist, contact a licensed practitioner. If you have known sensitivity to any of the ingredients, please consult your licensed practitioner before use. If you are pregnant or nursing a baby, seek the advice of a health care professional before use.

Keep out of the reach of children.

STORAGE AND HANDLING

Protect from light and heat.

Tamper Evident

Do not use this product if tamper evident strip is broken or removed from base of cap.

QUESTIONS

To report adverse events, contact BioResource at 321B Blodgett Street, Cotati, CA 94931

Distributed by:
BioResource Inc.
Cotati, CA 94931

Manufactured by:
PEKANA® GmbH
D-88353 Kisslegg

PRINCIPAL DISPLAY PANEL - 50 ml Bottle Box

CLAUPAREST™
Oral Drops

Homeopathic Medicine

For relief of minor
lower body stiffness
and pain

1.7 FL OZ
(50 ml)

PEKANA®